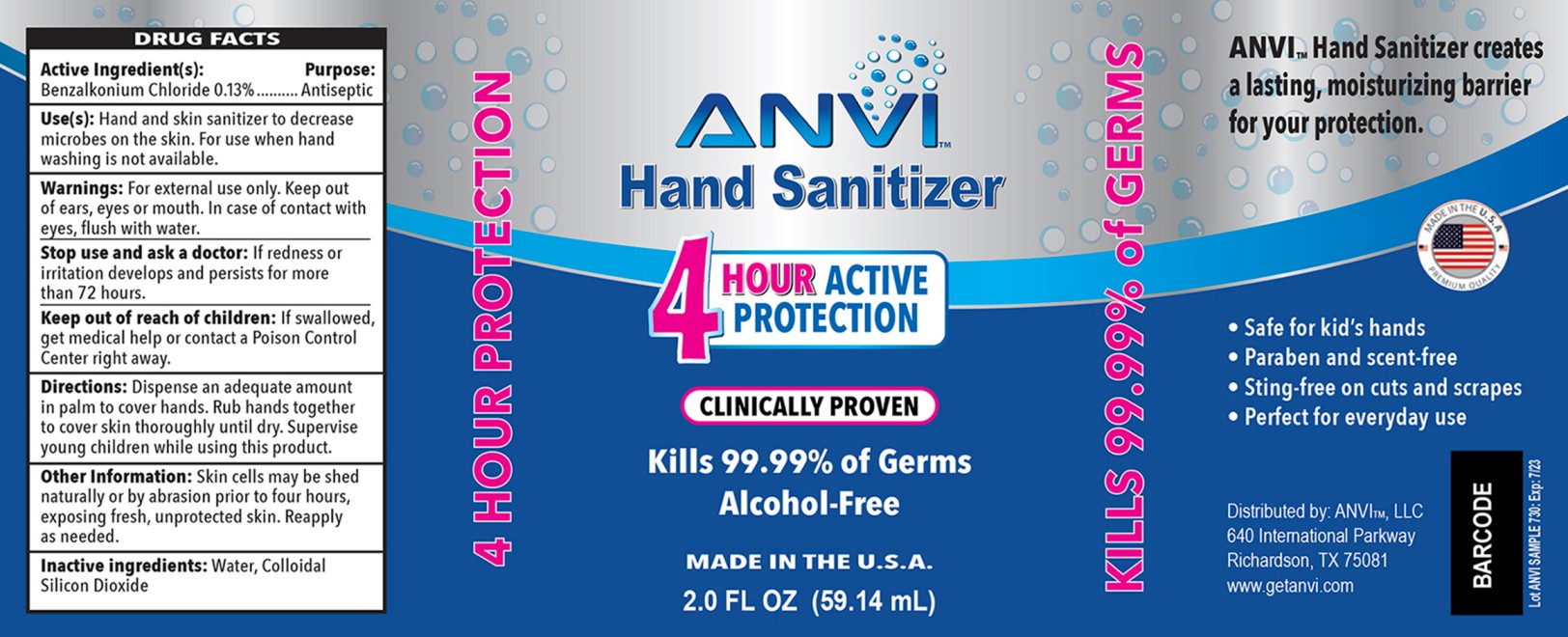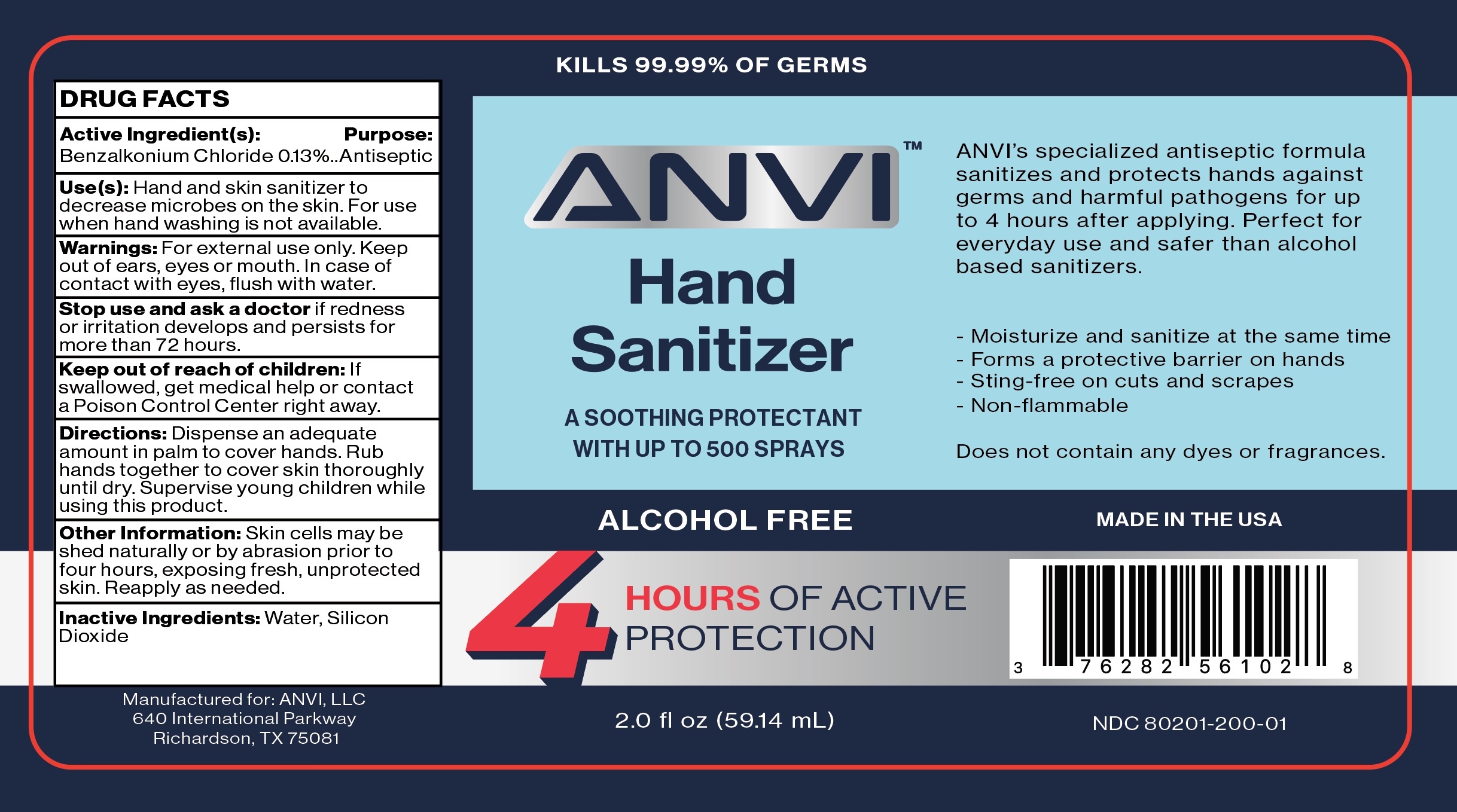 DRUG LABEL: Anvi
NDC: 80201-200 | Form: LIQUID
Manufacturer: Anvi LLC
Category: otc | Type: HUMAN OTC DRUG LABEL
Date: 20201117

ACTIVE INGREDIENTS: BENZALKONIUM CHLORIDE 0.13 g/100 mL
INACTIVE INGREDIENTS: SILICON DIOXIDE 0.2 g/100 mL; WATER 99.67 g/100 mL

Anvi

Active Ingredient(s)

Benzalkonium Chloride .13%..... Antiseptic

Purpose

Antiseptic, Hand Sanitizer

Use(s)

Hand and skin sanitizer to decrease microbes on the skin. For use when hand washing is not available.

Warnings

For external use only. Keep out of ears, eyes or mouth. In case of contact with eyes, flush with water.

Stop use and ask doctor: If redness or irritation develops and persists for more than 72 hours.

Keep out of reach of children: If swallowed, get medical help or contact a Cpoison Control Center right away.

Do not use

Stop use and ask a doctor: If redenss or irritation develops and persists for more than 72 hours.

Directions

Directions: Dispense an adequate amount into palm to cover hands. Rub hands together to cover skin thoroughly until dry. Supervise young children while using this product.

Other Information: Skin cells may shed naturally or by abrasion prior to four hours, exposing fresh, unprotected skin. Reapply as needed.

Stop use and ask a doctor: If redness or irritation develops and persists for more than 72 hours.

Keep out of reach of children: If swallowed, get medical help or contact a Poison Control Center right away.

Directions: Dispense an adequate amount into palm to cover hands. Rub hands together to cover skin thoroughly until dry. Supervise young children while using this product.

Directions for Use

Directions: Dispense an adequate amount into palm to cover hands. Rub hands together to cover skin thoroughly until dry. Supervise young children while using this product.

Other Information: Skin cells may shed naturally or by abrasion prior to four hours, exposing fresh, unprotected skin. Reapply as needed.

Other information

Other Information: Skin cells may shed naturally or by abrasion prior to four hours, exposing fresh, unprotected skin. Reapply as needed.

Inactive ingredients

Water. Colloidal Silicon Dioxide

Questions-Information

www.getanvi.com

Principal Display Panel

2 oz (59.14 mL) NDC 80201-100-01